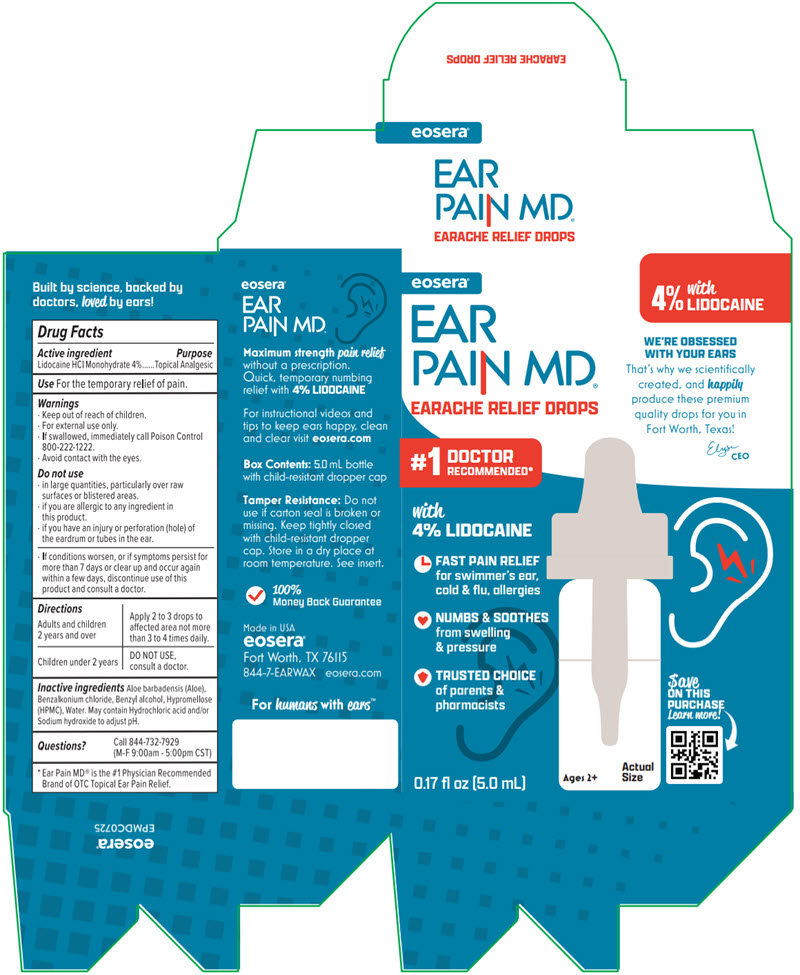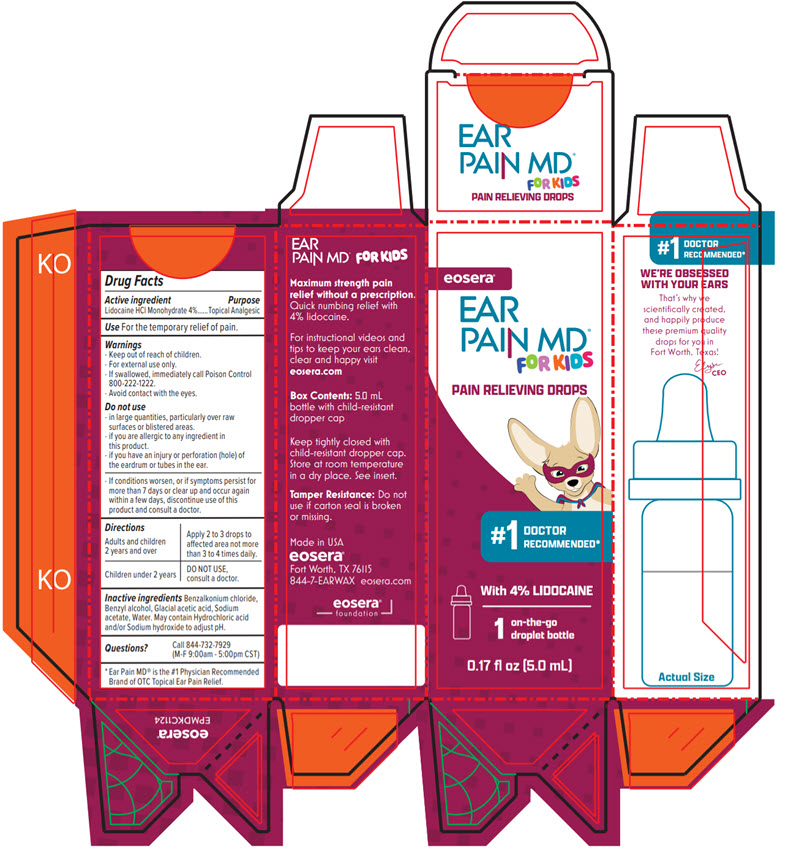 DRUG LABEL: Ear Pain MD
NDC: 72429-0001 | Form: LIQUID
Manufacturer: Eosera Inc
Category: otc | Type: HUMAN OTC DRUG LABEL
Date: 20251017

ACTIVE INGREDIENTS: LIDOCAINE HYDROCHLORIDE 4 g/100 mL
INACTIVE INGREDIENTS: ALOE VERA LEAF; BENZYL ALCOHOL; BENZALKONIUM CHLORIDE; HYPROMELLOSE, UNSPECIFIED; WATER

Ear Pain MD®

Drug Facts

Active ingredient

Lidocaine HCl Monohydrate 4%

Purpose

Topical Analgesic

Use

For the temporary relief of pain.

Warnings

- Keep out of reach of children.

- For external use only.
- If swallowed, immediately call Poison Control 800-222-1222.
- Avoid contact with the eyes.

Do not use

- in large quantities, particularly over raw surfaces or blistered areas.
- if you are allergic to any ingredient in this product.
- if you have an injury or perforation (hole) of the eardrum or tubes in the ear.

ASK DOCTOR

- If conditions worsen, or if symptoms persist for more than 7 days or clear up and occur again within a few days, discontinue use of this product and consult a doctor.

Directions

Adults and children 2 years and over | Apply 2 to 3 drops to affected area not more than 3 to 4 times daily.
Children under 2 years | Consult a doctor.

Inactive ingredients

Aloe barbadensis (Aloe), Benzalkonium chloride, Benzyl alcohol, Hypromellose (HPMC), Water. May contain hydrochloric acid and/or sodium hydroxide to adjust pH.

Questions?

Call 844-732-7929 (M-F 9:00am - 5:00pm CST)

PRINCIPAL DISPLAY PANEL - 5.0 mL Bottle Carton

eosera®

EAR
PAIN MD®

EARACHE RELIEF DROPS

#1
DOCTOR
RECOMMENDED*

with
4% LIDOCAINE

FAST PAIN RELIEF
for swimmer's ear,
cold & flu, allergies

NUMBS & SOOTHES
from swelling
& pressure

TRUSTED CHOICE
of parents &
pharmacists

0.17 fl oz (5.0 mL)

PRINCIPAL DISPLAY PANEL - 5.0 mL Bottle Carton - Kids

eosera®

EAR
PAIN MD®
FOR KIDS

PAIN RELIEVING DROPS

#1
DOCTOR
RECOMMENDED*

with 4% LIDOCAINE

1
on-the-go
droplet bottle

0.17 fl oz (5.0 mL)